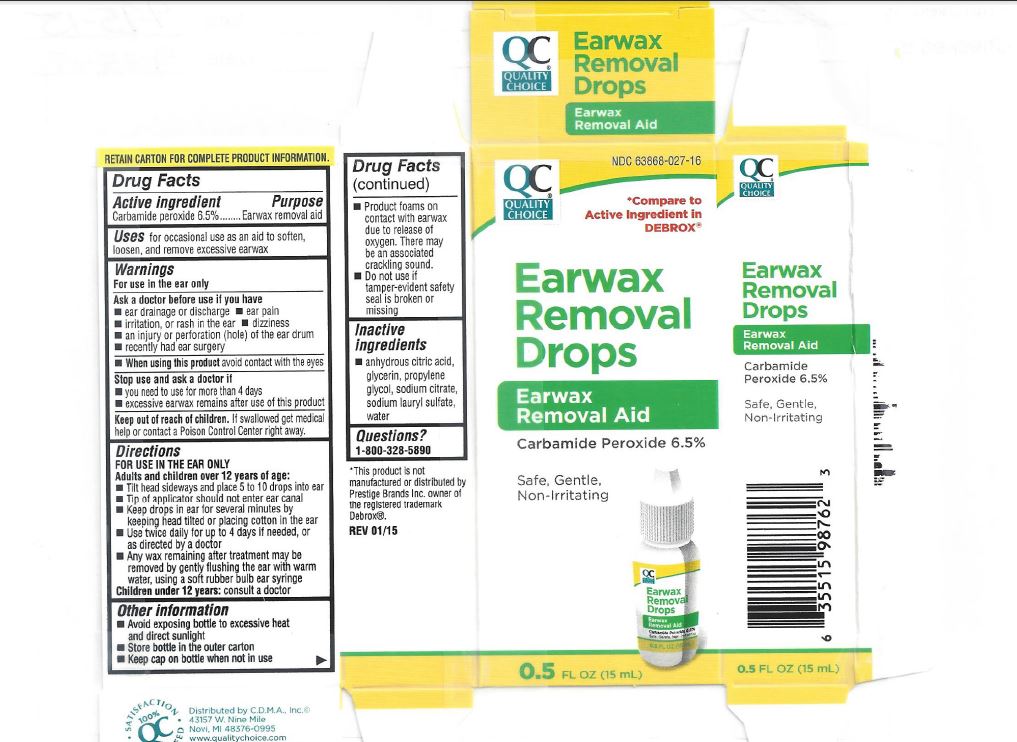 DRUG LABEL: Quality Choice Earwax Removal Drops
NDC: 63868-027 | Form: LIQUID
Manufacturer: Chain Drug Marketing Association, Inc.
Category: otc | Type: HUMAN OTC DRUG LABEL
Date: 20231215

ACTIVE INGREDIENTS: CARBAMIDE PEROXIDE 65 mg/1 mL
INACTIVE INGREDIENTS: ANHYDROUS CITRIC ACID; GLYCERIN; PROPYLENE GLYCOL; SODIUM CITRATE; SODIUM LAURYL SULFATE; WATER

Quality Choice Earwax Removal Drops

Active ingredient

Carbamide peroxide 6.5%

Purpose

Earwax removal aid

Uses

for occasional use as an aid to soften, looser, and remove excessive earwax

Warnings

For use in the ear only

Ask a doctor before use if you have

- Ear drainage or discharge
- Ear pain
- Irritation, or rash in the ear
- Dizziness
- An injury or perforation (hole) of the ear drum
- Recently had ear surgery

When using this product

avoid contact with the eyes

Stop use and ask a doctor if

- You need to use for more than 4 days
- Excessive earwax remains after use of this product

Keep out of reach of children

If swallowed get medical help or contact a Poison Control Center right away.

Directions

FOR USE IN THE EAR ONLYAdults and children over 12 years of age:

Children under 12 years: consult a doctor

- Tilt head sideways and place 5 to 10 drops into ear
- Tip of applicator should not enter ear canal
- Keep drops in ear for several minutes by keeping head titled or placing cotton in the ear
- Use twice daily for up to 4 days if needed, or as directed by a doctor
- Any wax remaining after treatment may be removed by gently flushing the ear with warm water, using a soft rubber bulb ear syringe

Other information

- Avoid exposing bottle to excessive heat and direct sunlight
- Store bottle in the outer carton
- Keep cap on bottle when not in use
- Product foams on contact with earwax due to release of oxygen. There may be an associated crackling sound
- Do not use if tamper-evident safety seal is broken or missing

Inactive ingredients

anhydrous citric acid, glycerin, propylene glycol, sodium citrate, sodium lauryl sulfate, water

Questions?

1-800-328-5890

*This product is not manufactured or distributed by Prestige Brands Inc. owner of the registered trademark Debrox. Distributed by C.D.M.A., Inc. 43157 W. Nine Mile Novi, MI 48376-0995 www.qualitychoice.com Questions: 248-449-9300

PACKAGE LABEL

Quality Choice Earwax Removal Drops Earwax Removal Aid Carbamide Peroxide 6.5% Safe, Gentle, Non-Irritating 0.5 FL OZ (15mL)